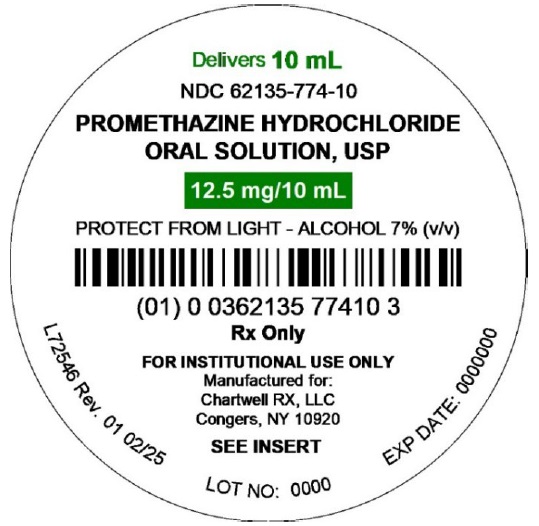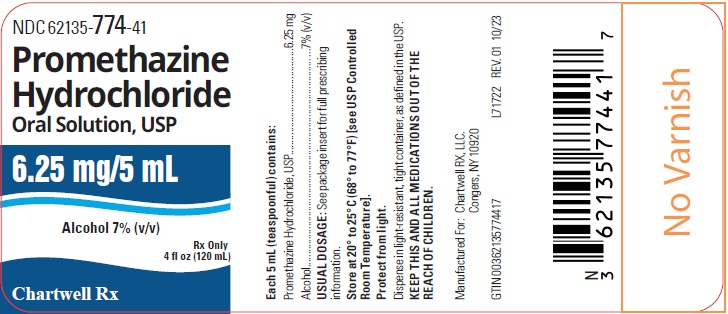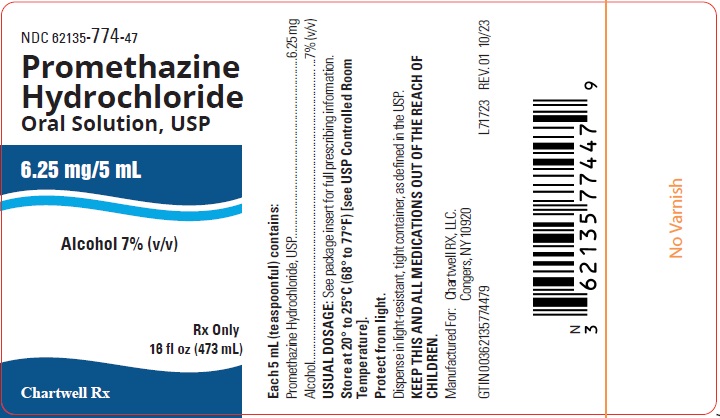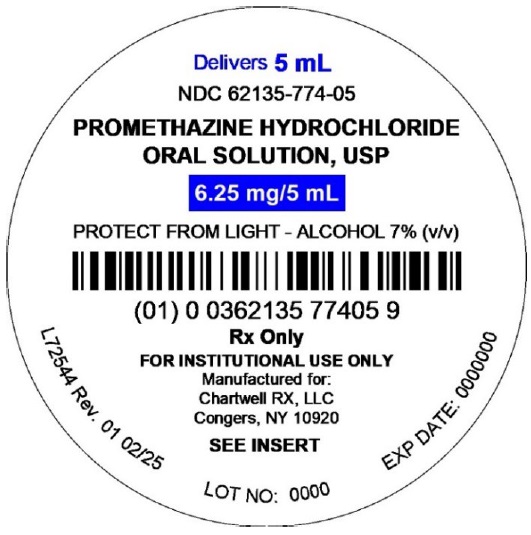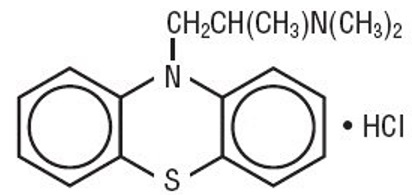 DRUG LABEL: PROMETHAZINE HYDROCHLORIDE
NDC: 62135-774 | Form: SOLUTION
Manufacturer: Chartwell RX, LLC
Category: prescription | Type: HUMAN PRESCRIPTION DRUG LABEL
Date: 20260130

ACTIVE INGREDIENTS: PROMETHAZINE HYDROCHLORIDE 6.25 mg/5 mL
INACTIVE INGREDIENTS: ALCOHOL; ASCORBIC ACID; ANHYDROUS CITRIC ACID; D&C YELLOW NO. 10; FD&C BLUE NO. 1; FD&C YELLOW NO. 6; FD&C RED NO. 40; METHYLPARABEN; PROPYLENE GLYCOL; PROPYLPARABEN; WATER; SACCHARIN SODIUM; SODIUM BENZOATE; SUCROSE; TRISODIUM CITRATE DIHYDRATE

PROMETHAZINE HYDROCHLORIDE ORAL SOLUTION, USP

DESCRIPTION

Each 5 mL (teaspoonful) of Promethazine Hydrochloride Oral Solution, USP contains: 6.25 mg of Promethazine Hydrochloride, USP.

The inactive ingredients present are alcohol 7%, ascorbic acid, citric acid anhydrous, D&C Yellow No. 10, FD&C Red No. 40, FD&C Blue No. 1, FD&C Yellow No. 6, methylparaben, natural cherry flavor, propylene glycol, propylparaben, purified water, saccharin sodium, sodium benzoate, sodium citrate dihydrate, and sucrose. Citric acid anhydrous or sodium citrate dihydrate is used to adjust the pH to 4.6 to 5.0.

Promethazine Hydrochloride, USP is a racemic compound; the empirical formula is C17H20N2S•HCl and its molecular weight is 320.88.

Promethazine Hydrochloride, USP, a phenothiazine derivative, is designated chemically as 10H-Phenothiazine-10-ethanamine,N,N,á-trimethyl-, monohydrochloride,(±)-, with the following structural formula:

Promethazine Hydrochloride, USP occurs as a white to faint yellow, practically odorless, crystalline powder which slowly oxidizes and turns blue on prolonged exposure to air. It is freely soluble in water and soluble in alcohol.

CLINICAL PHARMACOLOGY

Promethazine is a phenothiazine derivative which differs structurally from the antipsychotic phenothiazines by the presence of a branched side chain and no ring substitution. It is thought that this configuration is responsible for its relative lack (1/10 that of chlorpromazine) of dopamine antagonist properties.

Promethazine is an H1 receptor blocking agent. In addition to its antihistaminic action, it provides clinically useful sedative and antiemetic effects.

Promethazine is well absorbed from the gastrointestinal tract. Clinical effects are apparent within 20 minutes after oral administration and generally last four to six hours, although they may persist as long as 12 hours. Promethazine is metabolized by the liver to a variety of compounds; the sulfoxides of promethazine and N-demethylpromethazine are the predominant metabolites appearing in the urine.

INDICATIONS AND USAGE

Promethazine is useful for:

Perennial and seasonal allergic rhinitis.

Vasomotor rhinitis.

Allergic conjunctivitis due to inhalant allergens and foods.

Mild, uncomplicated skin manifestations of urticaria and angioedema.

Amelioration of allergic reactions to blood or plasma.

Dermographism.

Anaphylactic reactions, as adjunctive therapy to epinephrine and other standard measures, after the acute manifestations have been controlled.

Preoperative, postoperative or obstetric sedation.

Prevention and control of nausea and vomiting associated with certain types of anesthesia and surgery.

Therapy adjunctive to meperidine or other analgesics for control of postoperative pain.

Sedation in both children and adults, as well as relief of apprehension and production of light sleep from which the patient can be easily aroused.

Active and prophylactic treatment of motion sickness.

Antiemetic therapy in postoperative patients.

CONTRAINDICATIONS

Promethazine is contraindicated for use in pediatric patients less than two years of age.

Promethazine is contraindicated in comatose states, and in individuals known to be hypersensitive or to have had an idiosyncratic reaction to promethazine or to other phenothiazines.

Antihistamines are contraindicated for use in the treatment of lower respiratory tract symptoms including asthma.

WARNINGS

BOXED WARNING

PROMETHAZINE HYDROCHLORIDE ORAL SOLUTION SHOULD NOT BE USED IN PEDIATRIC PATIENTS LESS THAN 2 YEARS OF AGE BECAUSE OF THE POTENTIAL FOR FATAL RESPIRATORY DEPRESSION.

POSTMARKETING CASES OF RESPIRATORY DEPRESSION, INCLUDING FATALITIES, HAVE BEEN REPORTED WITH USE OF PROMETHAZINE HYDROCHLORIDE ORAL SOLUTION IN PEDIATRIC PATIENTS LESS THAN 2 YEARS OF AGE. A WIDE RANGE OF WEIGHT-BASED DOSES OF PROMETHAZINE HYDROCHLORIDE ORAL SOLUTION HAVE RESULTED IN RESPIRATORY DEPRESSION IN THESE PATIENTS.

CAUTION SHOULD BE EXERCISED WHEN ADMINISTERING PROMETHAZINE HYDROCHLORIDE ORAL SOLUTION TO PEDIATRIC PATIENTS 2 YEARS OF AGE AND OLDER. IT IS RECOMMENDED THAT THE LOWEST EFFECTIVE DOSE OF PROMETHAZINE HYDROCHLORIDE ORAL SOLUTION BE USED IN PEDIATRIC PATIENTS 2 YEARS OF AGE AND OLDER AND CONCOMITANT ADMINISTRATION OF OTHER DRUGS WITH RESPIRATORY DEPRESSANT EFFECTS BE AVOIDED.

CNS Depression

Promethazine may impair the mental and/or physical abilities required for the performance of potentially hazardous tasks, such as driving a vehicle or operating machinery. The impairment may be amplified by concomitant use of other central-nervous-system depressants such as alcohol, sedatives/hypnotics (including barbiturates), narcotics, narcotic analgesics, general anesthetics, tricyclic antidepressants, and tranquilizers; therefore such agents should either be eliminated or given in reduced dosage in the presence of promethazine HCl (see PRECAUTIONS– Information for Patients and Drug Interactions).

Respiratory Depression

Promethazine may lead to potentially fatal respiratory depression.

Use of Promethazine in patients with compromised respiratory function (e.g., COPD, sleep apnea) should be avoided.

Lower Seizure Threshold

Promethazine may lower seizure threshold. It should be used with caution in persons with seizure disorders or in persons who are using concomitant medications, such as narcotics or local anesthetics, which may also affect seizure threshold.

Bone-Marrow Depression

Promethazine should be used with caution in patients with bone-marrow depression. Leukopenia and agranulocytosis have been reported, usually when promethazine HCl has been used in association with other known marrow-toxic agents.

Neuroleptic Malignant Syndrome

A potentially fatal symptom complex sometimes referred to as Neuroleptic Malignant Syndrome (NMS) has been reported in association with promethazine HCl alone or in combination with antipsychotic drugs. Clinical manifestations of NMS are hyperpyrexia, muscle rigidity, altered mental status and evidence of autonomic instability (irregular pulse or blood pressure, tachycardia, diaphoresis and cardiac dysrhythmias).

The diagnostic evaluation of patients with this syndrome is complicated. In arriving at a diagnosis, it is important to identify cases where the clinical presentation includes both serious medical illness (e.g., pneumonia, systemic infection, etc.) and untreated or inadequately treated extrapyramidal signs and symptoms (EPS). Other important considerations in the differential diagnosis include central anticholinergic toxicity, heat stroke, drug fever and primary central nervous system (CNS) pathology.

The management of NMS should include 1) immediate discontinuation of promethazine HCl, antipsychotic drugs, if any, and other drugs not essential to concurrent therapy, 2) intensive symptomatic treatment and medical monitoring, and 3) treatment of any concomitant serious medical problems for which specific treatments are available. There is no general agreement about specific pharmacological treatment regimens for uncomplicated NMS.

Since recurrences of NMS have been reported with phenothiazines, the reintroduction of promethazine HCl should be carefully considered.

Use in Pediatric Patients

PROMETHAZINE HYDROCHLORIDE ORAL SOLUTION IS CONTRAINDICATED FOR USE IN PEDIATRIC PATIENTS LESS THAN TWO YEARS OF AGE.

CAUTION SHOULD BE EXERCISED WHEN ADMINISTERING PROMETHAZINE HYDROCHLORIDE ORAL SOLUTION TO PEDIATRIC PATIENTS 2 YEARS OF AGE AND OLDER BECAUSE OF THE POTENTIAL FOR FATAL RESPIRATORY DEPRESSION. RESPIRATORY DEPRESSION AND APNEA, SOMETIMES ASSOCIATED WITH DEATH, ARE STRONGLY ASSOCIATED WITH PROMETHAZINE PRODUCTS AND ARE NOT DIRECTLY RELATED TO INDIVIDUALIZED WEIGHT-BASED DOSING, WHICH MIGHT OTHERWISE PERMIT SAFE ADMINISTRATION. CONCOMITANT ADMINISTRATION OF PROMETHAZINE PRODUCTS WITH OTHER RESPIRATORY DEPRESSANTS HAS AN ASSOCIATION WITH RESPIRATORY DEPRESSION, AND SOMETIMES DEATH, IN PEDIATRIC PATIENTS.

ANTIEMETICS ARE NOT RECOMMENDED FOR TREATMENT OF UNCOMPLICATED VOMITING IN PEDIATRIC PATIENTS, AND THEIR USE SHOULD BE LIMITED TO PROLONGED VOMITING OF KNOWN ETIOLOGY. THE EXTRAPYRAMIDAL SYMPTOMS WHICH CAN OCCUR SECONDARY TO PROMETHAZINE HYDROCHLORIDE ORAL SOLUTION ADMINISTRATION MAY BE CONFUSED WITH THE CNS SIGNS OF UNDIAGNOSED PRIMARY DISEASE, e.g., ENCEPHALOPATHY OR REYE’S SYNDROME. THE USE OF PROMETHAZINE HYDROCHLORIDE ORAL SOLUTION SHOULD BE AVOIDED IN PEDIATRIC PATIENTS WHOSE SIGNS AND SYMPTOMS MAY SUGGEST REYE’S SYNDROME OR OTHER HEPATIC DISEASES.

Excessively large dosages of antihistamines, including Promethazine Hydrochloride Oral Solution, in pediatric patients may cause sudden death (see OVERDOSAGE). Hallucinations and convulsions have occurred with therapeutic doses and overdoses of Promethazine in pediatric patients. In pediatric patients who are acutely ill associated with dehydration, there is an increased susceptibility to dystonias with the use of promethazine HCl.

Other Considerations

Administration of promethazine HCl has been associated with reported cholestatic jaundice.

PRECAUTIONS

General

Drugs having anticholinergic properties should be used with caution in patients with narrow-angle glaucoma, prostatic hypertrophy, stenosing peptic ulcer, pyloroduodenal obstruction, and bladder-neck obstruction. Promethazine should be used cautiously in persons with cardiovascular disease or with impairment of liver function.

Information for Patients

Promethazine may cause marked drowsiness or impair the mental and/or physical abilities required for the performance of potentially hazardous tasks, such as driving a vehicle or operating machinery. The use of alcohol or other central-nervous-system depressants such as sedatives/ hypnotics (including barbiturates), narcotics, narcotic analgesics, general anesthetics, tricyclic antidepressants, and tranquilizers, may enhance impairment (see WARNINGS- CNS Depressionand PRECAUTIONS- Drug Interactions). Pediatric patients should be supervised to avoid potential harm in bike riding or in other hazardous activities.

Patients should be advised to report any involuntary muscle movements.

Avoid prolonged exposure to the sun.

Drug Interactions

CNS Depressants- Promethazine may increase, prolong, or intensify the sedative action of other central-nervous-system depressants, such as alcohol, sedatives/hypnotics (including barbiturates), narcotics, narcotic analgesics, general anesthetics, tricyclic antidepressants, and tranquilizers; therefore, such agents should be avoided or administered in reduced dosage to patients receiving promethazine HCl. When given concomitantly with Promethazine Hydrochloride Oral Solution, the dose of barbiturates should be reduced by at least one-half, and the dose of narcotics should be reduced by one-quarter to one-half. Dosage must be individualized. Excessive amounts of promethazine HCl relative to a narcotic may lead to restlessness and motor hyperactivity in the patient with pain; these symptoms usually disappear with adequate control of the pain.

Epinephrine

Because of the potential for Promethazine to reverse epinephrine’s vasopressor effect, epinephrine should NOT be used to treat hypotension associated with Promethazine Hydrochloride Oral Solution overdose.

Anticholinergics

Concomitant use of other agents with anticholinergic properties should be undertaken with caution.

Monoamine Oxidase Inhibitors (MAOI)

Drug interactions, including an increased incidence of extrapyramidal effects, have been reported when some MAOI and phenothiazines are used concomitantly. This possibility should be considered with Promethazine Hydrochloride Oral Solution.

Drug/Laboratory Test Interactions

The following laboratory tests may be affected in patients who are receiving therapy with promethazine HCl:

Pregnancy Tests

Diagnostic pregnancy tests based on immunological reactions between HCG and anti-HCG may result in false-negative or false-positive interpretations.

Glucose Tolerance Test

An increase in blood glucose has been reported in patients receiving promethazine.

Carcinogenesis, Mutagenesis, Impairment of Fertility

Long-term animal studies have not been performed to assess the carcinogenic potential of promethazine, nor are there other animal or human data concerning carcinogenicity, mutagenicity, or impairment of fertility with this drug. Promethazine was nonmutagenic in the Salmonella test system of Ames.

Pregnancy

Teratogenic Effects

Teratogenic effects have not been demonstrated in rat-feeding studies at doses of 6.25 and 12.5 mg/kg of promethazine HCl. These doses are from approximately 2.1 to 4.2 times the maximum recommended total daily dose of promethazine for a 50-kg subject, depending upon the indication for which the drug is prescribed. Daily doses of 25 mg/kg intraperitoneally have been found to produce fetal mortality in rats.

Specific studies to test the action of the drug on parturition, lactation, and development of the animal neonate were not done, but a general preliminary study in rats indicated no effect on these parameters. Although antihistamines, including promethazine, have been found to produce fetal mortality in rodents, the pharmacological effects of histamine in the rodent do not parallel those in man. There are no adequate and well-controlled studies of promethazine in pregnant women.

Promethazine should be used during pregnancy only if the potential benefit justifies the potential risk to the fetus.

Nonteratogenic Effects

Promethazine administered to a pregnant woman within two weeks of delivery may inhibit platelet aggregation in the newborn.

Labor and Delivery

Promethazine HCl, may be used alone or as an adjunct to narcotic analgesics during labor (see " DOSAGE AND ADMINISTRATION"). Limited data suggest that use of Promethazine during labor and delivery does not have an appreciable effect on the duration of labor and delivery and does not increase the risk of need for intervention in the newborn. The effect on later growth and development of the newborn is unknown. (See also Nonteratogenic Effects.)

Nursing Mothers

It is not known whether promethazine HCl is excreted in human milk. Because many drugs are excreted in human milk and because of the potential for serious adverse reactions in nursing infants from Promethazine Hydrochloride Oral Solution, a decision should be made whether to discontinue nursing or to discontinue the drug, taking into account the importance of the drug to the mother.

Pediatric Use

PROMETHAZINE HYDROCHLORIDE ORAL SOLUTION IS CONTRAINDICATED FOR USE IN PEDIATRIC PATIENTS LESS THAN TWO YEARS OF AGE (see WARNINGS- Black Box Warningand Use in Pediatric Patients). Promethazine Hydrochloride Oral Solution should be used with caution in pediatric patients 2 years of age and older (see WARNINGS- Use in Pediatric Patients).

Geriatric Use

Clinical studies of Promethazine formulations did not include sufficient numbers of subjects aged 65 and over to determine whether they respond differently from younger subjects. Other reported clinical experience has not identified differences in responses between the elderly and younger patients. In general, dose selection for an elderly patient should be cautious, usually starting at the low end of the dosing range, reflecting the greater frequency of decreased hepatic, renal or cardiac function, and of concomitant disease or other drug therapy.

Sedating drugs may cause confusion and over-sedation in the elderly; elderly patients generally should be started on low doses of Promethazine and observed closely.

ADVERSE REACTIONS

To report SUSPECTED ADVERSE REACTIONS, contact Chartwell RX, LLC. at 1-845-232-1683 or FDA at 1-800-FDA-1088 or www.fda.gov/medwatch.

Central Nervous System

Drowsiness is the most prominent CNS effect of this drug. Sedation, somnolence, blurred vision, dizziness; confusion, disorientation, and extrapyramidal symptoms such as oculogyric crisis, torticollis, and tongue protrusion; lassitude, tinnitus, incoordination, fatigue, euphoria, nervousness, diplopia, insomnia, tremors, convulsive seizures, excitation, catatonic-like states, hysteria. Hallucinations have also been reported.

Cardiovascular

Increased or decreased blood pressure, tachycardia, bradycardia, faintness.

Dermatologic

Dermatitis, photosensitivity, urticaria. Hematologic–Leukopenia, thrombocytopenia, thrombocytopenic purpura, agranulocytosis.

Gastrointestinal

Dry mouth, nausea, vomiting, jaundice.

Respiratory

Asthma, nasal stuffiness, respiratory depression (potentially fatal) and apnea (potentially fatal). (See WARNINGS- Respiratory Depression.)

Other

Angioneurotic edema. Neuroleptic malignant syndrome (potentially fatal) has also been reported. (See WARNINGS- Neuroleptic Malignant Syndrome.)

Paradoxical Reactions

Hyperexcitability and abnormal movements have been reported in patients following a single administration of promethazine HCl. Consideration should be given to the discontinuation of promethazine HCl and to the use of other drugs if these reactions occur. Respiratory depression, nightmares, delirium, and agitated behavior have also been reported in some of these patients.

OVERDOSAGE

Signs and symptoms of overdosage with promethazine HCl range from mild depression of the central nervous system and cardiovascular system to profound hypotension, respiratory depression, unconsciousness and sudden death. Other reported reactions include hyperreflexia, hypertonia, ataxia, athetosis, and extensor-plantar reflexes (Babinski reflex).

Stimulation may be evident, especially in children and geriatric patients. Convulsions may rarely occur. A paradoxical-type reaction has been reported in children receiving single doses of 75 mg to 125 mg orally, characterized by hyperexcitability and nightmares.

Atropine-like signs and symptoms - dry mouth, fixed dilated pupils, flushing, as well as gastrointestinal symptoms - may occur.

Treatment

Treatment of overdosage is essentially symptomatic and supportive. Only in cases of extreme overdosage or individual sensitivity do vital signs including respiration, pulse, blood pressure, temperature, and EKG need to be monitored. Activated charcoal orally or by lavage may be given, or sodium or magnesium sulfate orally as a cathartic. Attention should be given to the reestablishment of adequate respiratory exchange through provision of a patent airway and institution of assisted or controlled ventilation. Diazepam may be used to control convulsions. Acidosis and electrolyte losses should be corrected. Note that any depressant effects of promethazine HCl are not reversed by naloxone. Avoid analeptics which may cause convulsions.

The treatment of choice for resulting hypotension is administration of intravenous fluids, accompanied by repositioning if indicated. In the event that vasopressors are considered for the management of severe hypotension which does not respond to intravenous fluids and repositioning, the administration of norepinephrine or phenylephrine should be considered. EPINEPHRINE SHOULD NOT BE USED, since its use in patients with partial adrenergic blockade may further lower the blood pressure.

Extrapyramidal reactions may be treated with anticholinergic antiparkinsonian agents, diphenhydramine, or barbiturates. Oxygen may also be administered.

Limited experience with dialysis indicates that it is not helpful.

DOSAGE AND ADMINISTRATION

Promethazine Hydrochloride Oral Solution is contraindicated for children under 2 years of age(see WARNINGS - Black Box Warning and Use in Pediatric Patients).

Allergy

The average oral dose is 25 mg taken before retiring; however, 12.5 mg may be taken before meals and on retiring, if necessary. Children tolerate this product well. Single 25 mg doses at bedtime or 6.25 to 12.5 mg taken three times daily will usually suffice. After initiation of treatment in children or adults, dosage should be adjusted to the smallest amount adequate to relieve symptoms.

The administration of promethazine HCl in 25 mg doses will control minor transfusion reactions of an allergic nature.

Motion Sickness

The average adult dose is 25 mg taken twice daily. The initial dose should be taken one-half to one hour before anticipated travel and be repeated 8 to 12 hours later, if necessary. On succeeding days of travel, it is recommended that 25 mg be given on arising and again before the evening meal. For children, promethazine hydrochloride tablets, oral solution or rectal suppositories 12.5 to 25 mg, twice daily, may be administered.

Nausea and Vomiting

Antiemetics should not be used in vomiting of unknown etiology in children and adolescents (see WARNINGS- Use in Pediatric Patients).

The average effective dose of promethazine hydrochloride for the active therapy of nausea and vomiting in children or adults is 25 mg. When oral medication cannot be tolerated, the dose should be given parenterally (cf. Promethazine Hydrochloride Injection) or by rectal suppository. 12.5 to 25 mg doses may be repeated, as necessary, at 4 to 6 hour intervals.

For nausea and vomiting in children, the usual dose is 0.5 mg per pound of body weight, and the dose should be adjusted to the age and weight of the patient and the severity of the condition being treated.

For prophylaxis of nausea and vomiting, as during surgery and the post-operative period, the average dose is 25 mg repeated at 4 to 6 hour intervals, as necessary.

Sedation

This product relieves apprehension and induces a quiet sleep from which the patient can be easily aroused. Administration of 12.5 to 25 mg promethazine hydrochloride by the oral route or by rectal suppository at bedtime will provide sedation in children. Adults usually require 25 to 50 mg for nighttime, presurgical, or obstetrical sedation.

Pre-and Postoperative Use

Promethazine hydrochloride in 12.5 to 25 mg doses for children and 50 mg doses for adults the night before surgery relieves apprehension and produces a quiet sleep.

For preoperative medication children require doses of 0.5 mg per pound of body weight in combination with an appropriately reduced dose of narcotic or barbiturate and the appropriate dose of an atropine-like drug.

Usual adult dosage is 50 mg promethazine hydrochloride with an appropriately reduced dose of narcotic or barbiturate and the required amount of a belladonna alkaloid.

Postoperative sedation and adjunctive use with analgesics may be obtained by the administration of 12.5 to 25 mg in children and 25 to 50 mg doses in adults.

Promethazine Hydrochloride Oral Solution is contraindicated for children under 2 years of age.

HOW SUPPLIED

Promethazine Hydrochloride Oral Solution, USP 6.25 mg/ 5mL is a green colored viscous syrup with a light cherry odor is supplied as follows:

Bottle of 120 mL – NDC 62135-774-41

Bottle of 473 mL – NDC 62135-774-47

Unit Dose Cup of 5 mL – NDC 62135-774-05

20 Unit Dose Cups of 5 mL – NDC 62135-774-24

Unit Dose Cup of 10 mL – NDC 62135-774-10

20 Unit Dose Cups of 10 mL – NDC 62135-774-23

Keep tightly closed.

Store at 20° to 25°C (68° to 77°F) [see USP Controlled Room Temperature].

Protect from light.

Dispense in light-resistant, tight container.

Manufactured for:
Chartwell RX, LLC.
Congers, NY 10920

Rev: 01/2026

L71724

PACKAGE LABEL.PRINCIPAL DISPLAY PANEL

Promethazine Hydrochloride Oral Solution, USP 6.25 mg/5 mL - NDC 62135-774-41 - 120 mL Bottle Label

Promethazine Hydrochloride Oral Solution, USP 6.25 mg/5 mL - NDC 62135-774-47 - 473 mL Bottle Label

Promethazine Hydrochloride Oral Solution, USP 6.25 mg/5 mL - NDC 62135-774-05 - 5 mL Cup Label

Promethazine Hydrochloride Oral Solution, USP 12.5 mg/10 mL - NDC 62135-774-10 - 10 mL Cup Label